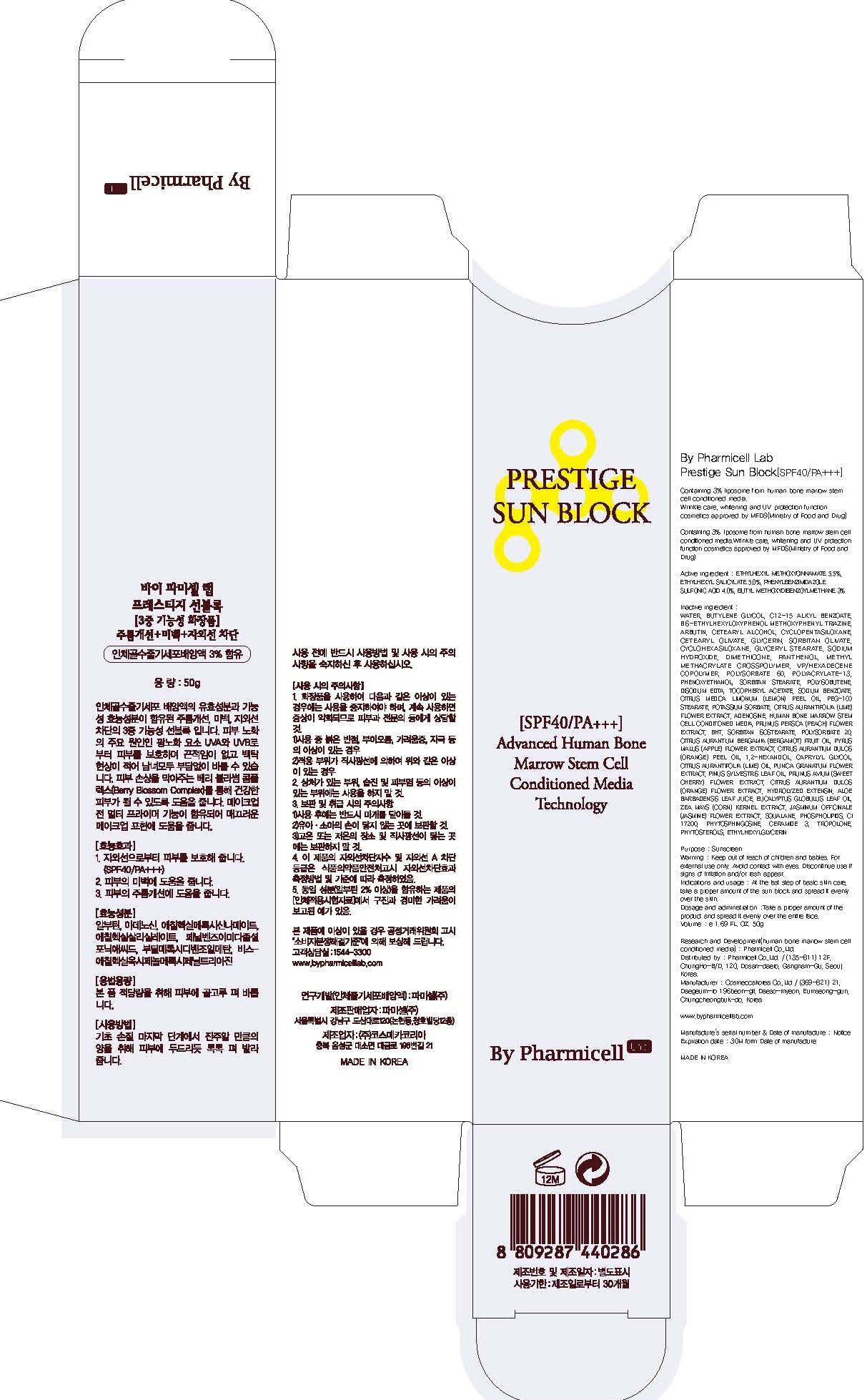 DRUG LABEL: By Pharmicell Lab Prestige Sun Block
NDC: 60949-030 | Form: CREAM
Manufacturer: Pharmicell Co., Ltd.
Category: otc | Type: HUMAN OTC DRUG LABEL
Date: 20131119

ACTIVE INGREDIENTS: OCTINOXATE 2.75 g/50 g; OCTISALATE 2.5 g/50 g; ENSULIZOLE 2 g/50 g; AVOBENZONE 1.5 g/50 g
INACTIVE INGREDIENTS: WATER; BUTYLENE GLYCOL

ACTIVE INGREDIENT

Active ingredient : OCTINOXATE 5.5%, OCTISALATE 5.0%, ENSULIZOLE 4.0%, AVOBENZONE 3%

INACTIVE INGREDIENT

Inactive ingredient : WATER, BUTYLENE GLYCOL, C12-15 ALKYL BENZOATE, BIS-ETHYLHEXYLOXYPHENOL METHOXYPHENYL TRIAZINE, ARBUTIN, CETEARYL ALCOHOL, CYCLOPENTASILOXANE, CETEARYL OLIVATE, GLYCERIN, SORBITAN OLIVATE, CYCLOHEXASILOXANE, GLYCERYL STEARATE, SODIUM HYDROXIDE, DIMETHICONE, PANTHENOL, METHYL METHACRYLATE CROSSPOLYMER, VP/HEXADECENE COPOLYMER, POLYSORBATE 60, POLYACRYLATE-13, PHENOXYETHANOL, SORBITAN STEARATE, POLYISOBUTENE, DISODIUM EDTA, TOCOPHERYL ACETATE, SODIUM BENZOATE, CITRUS MEDICA LIMONUM (LEMON) PEEL OIL, PEG-100 STEARATE, POTASSIUM SORBATE, CITRUS AURANTIFOLIA (LIME) FLOWER EXTRACT, ADENOSINE, HUMAN BONE MARROW STEM CELL CONDITIONED MEDIA, PRUNUS PERSICA (PEACH) FLOWER EXTRACT, BHT, SORBITAN ISOSTEARATE, POLYSORBATE 20, CITRUS AURANTIUM BERGAMIA (BERGAMOT) FRUIT OIL, PYRUS MALUS (APPLE) FLOWER EXTRACT, CITRUS AURANTIUM DULCIS (ORANGE) PEEL OIL, 1,2-HEXANDIOL, CAPRYLYL GLYCOL, CITRUS AURANTIFOLIA (LIME) OIL, PUNICA GRANATUM FLOWER EXTRACT, PINUS SYLVESTRIS LEAF OIL, PRUNUS AVIUM (SWEET CHERRY) FLOWER EXTRACT, CITRUS AURANTIUM DULCIS (ORANGE) FLOWER EXTRACT, HYDROLYZED EXTENSIN, ALOE BARBADENSIS LEAF JUICE, EUCALYPTUS GLOBULUS LEAF OIL, ZEA MAYS (CORN) KERNEL EXTRACT, JASMINUM OFFICINALE (JASMINE) FLOWER EXTRACT, SQUALANE, PHOSPHOLIPIDS, CI 17200, PHYTOSPHINGOSINE, CERAMIDE 3, TROPOLONE, PHYTOSTEROLS, ETHYLHEXYLGLYCERIN

PURPOSE

Purpose : Sunscreen

WARNINGS

Warning : Keep out of reach of children and babies. For external use only. Avoid contact with eyes. Discontinue use if signs of irritation and/or rash appear.

Keep out of reach of children and babies.

Indications and usage : At the last step of basic skin care, take a proper amount of the sun block and spread it evenly over the skin.

Dosage and administration : Take a proper amount of the product and spread it evenly over the entire face.